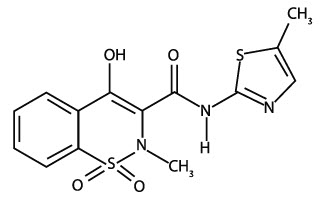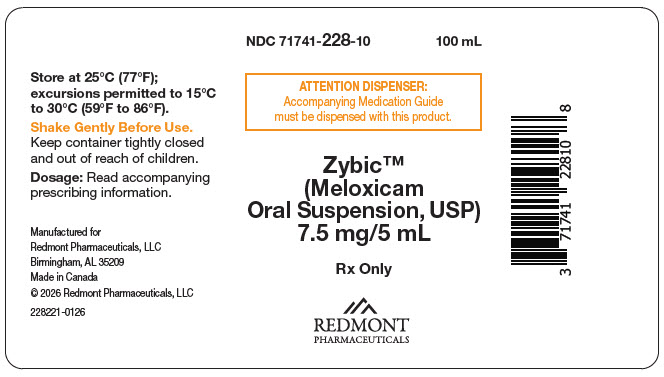 DRUG LABEL: Zybic
NDC: 71741-228 | Form: SUSPENSION
Manufacturer: Redmont Pharmaceuticals, LLC
Category: prescription | Type: HUMAN PRESCRIPTION DRUG LABEL
Date: 20241031

ACTIVE INGREDIENTS: Meloxicam 7.5 mg/5 mL
INACTIVE INGREDIENTS: Silicon Dioxide; HYDROXYETHYL CELLULOSE (2000 MPA.S AT 1%); Sorbitol; GLYCERIN; Xylitol; Sodium Phosphate, Monobasic, Dihydrate; Saccharin Sodium; Sodium Benzoate; Citric Acid Monohydrate; Water

HIGHLIGHTS OF PRESCRIBING INFORMATION

These highlights do not include all the information needed to use Zybic™ safely and effectively. See full prescribing information for Zybic™.
Zybic™
Initial U.S. Approval: 2004

WARNING: RISK OF SERIOUS CARDIOVASCULAR AND GASTROINTESTINAL EVENTS

See full prescribing information for complete boxed warning.

- Nonsteroidal anti-inflammatory drugs (NSAIDs) cause an increased risk of serious cardiovascular thrombotic events, including myocardial infarction and stroke, which can be fatal. This risk may occur early in treatment and may increase with duration of use (5.1)
- Zybic™ is contraindicated in the setting of coronary artery bypass graft (CABG) surgery (4, 5.1)
- NSAIDs cause an increased risk of serious gastrointestinal (GI) adverse events including bleeding, ulceration, and perforation of the stomach or intestines, which can be fatal. These events can occur at any time during use and without warning symptoms. Elderly patients and patients with a prior history of peptic ulcer disease and/or GI bleeding are at greater risk for serious GI events (5.2)

RECENT MAJOR CHANGES

Warnings and Precautions (5.10) | 10/2024

1 INDICATIONS AND USAGE

Zybic™ is a non-steroidal anti-inflammatory drug indicated for:

- Osteoarthritis (OA) (1.1)
- Rheumatoid Arthritis (RA) (1.2)
- Juvenile Rheumatoid Arthritis (JRA) in patients 2 years of age or older (1.3)

2 DOSAGE AND ADMINISTRATION

Use the lowest effective dosage for the shortest duration consistent with individual patient treatment goals (2.1)

- OA (2.2) and RA (2.3):
  - Starting dose: 7.5 mg once daily
  - Dose may be increased to 15 mg once daily
- JRA (2.4):
  - 0.125 mg/kg once daily up to a maximum of 7.5 mg. JRA dosing using the oral suspension should be individualized based on the weight of the child (2.4)
- Zybic™ is not interchangeable with approved formulations of oral meloxicam even if the total milligram strength is the same (2.6)

3 DOSAGE FORMS AND STRENGTHS

- Zybic™: 7.5 mg/5 mL (3)

4 CONTRAINDICATIONS

- Known hypersensitivity to meloxicam or any components of the drug product (4)
- History of asthma, urticaria, or other allergic-type reactions after taking aspirin or other NSAIDs (4)
- In the setting of CABG surgery (4)

5 WARNINGS AND PRECAUTIONS

- Hepatotoxicity: Inform patients of warning signs and symptoms of hepatotoxicity. Discontinue if abnormal liver tests persist or worsen or if clinical signs and symptoms of liver disease develop (5.3)
- Hypertension: Patients taking some antihypertensive medications may have impaired response to these therapies when taking NSAIDs. Monitor blood pressure (5.4, 7)
- Heart Failure and Edema: Avoid use of Zybic™ in patients with severe heart failure unless benefits are expected to outweigh risk of worsening heart failure (5.5)
- Renal Toxicity: Monitor renal function in patients with renal or hepatic impairment, heart failure, dehydration, or hypovolemia. Avoid use of Zybic™ in patients with advanced renal disease unless benefits are expected to outweigh risk of worsening renal function (5.6)
- Anaphylactic Reactions: Seek emergency help if an anaphylactic reaction occurs (5.7)
- Exacerbation of Asthma Related to Aspirin Sensitivity: Zybic™ is contraindicated in patients with aspirin-sensitive asthma. Monitor patients with preexisting asthma (without aspirin sensitivity) (5.8)
- Serious Skin Reactions: Discontinue Zybic™ at first appearance of skin rash or other signs of hypersensitivity (5.9)
- Drug Reaction with Eosinophilia and Systemic Symptoms (DRESS): Discontinue and evaluate clinically (5.10)
- Fetal Toxicity: Limit use of NSAIDs, including Zybic™, between about 20 to 30 weeks in pregnacy due to the risk of oligohydramnios/fetal renal dysfunction. Avoid use of NSAIDs in women at about 30 weeks gestation and later in pregnancy due to the risks of oligohydramnios/fetal renal dysfunction and premature closure of fetal ductus arteriosus (5.11, 8.1)
- Hematologic Toxicity: Monitor hemoglobin or hematocrit in patients with any signs or symptoms of anemia (5.12, 7)

6 ADVERSE REACTIONS

- Most common (≥5% and greater than placebo) adverse events in adults are diarrhea, upper respiratory tract infections, dyspepsia, and influenza-like symptoms (6.1)
- Adverse events observed in pediatric studies were similar in nature to the adult clinical trial experience (6.1)

To report SUSPECTED ADVERSE REACTIONS, contact Redmont Pharmaceuticals, LLC at (800) 528-3058 or FDA at 1-800-FDA-1088 or www.fda.gov/medwatch.

7 DRUG INTERACTIONS

- Drugs that Interfere with Hemostasis (e.g., warfarin, aspirin, SSRIs/SNRIs): Monitor patients for bleeding who are concomitantly taking Zybic™ with drugs that interfere with hemostasis. Concomitant use of Zybic™ and analgesic doses of aspirin is not generally recommended (7)
- ACE Inhibitors, Angiotensin Receptor Blockers (ARBs) or Beta-Blockers: Concomitant use with Zybic™ may diminish the antihypertensive effect of these drugs. Monitor blood pressure (7)
- ACE Inhibitors and ARBs: Concomitant use with Zybic™ in elderly, volume-depleted, or those with renal impairment may result in deterioration of renal function. In such high risk patients, monitor for signs of worsening renal function (7)
- Diuretics: NSAIDs can reduce natriuretic effect of furosemide and thiazide diuretics. Monitor patients to assure diuretic efficacy including antihypertensive effects (7)

8 USE IN SPECIFIC POPULATIONS

- Infertility: NSAIDs are associated with reversible infertility. Consider withdrawal of Zybic™ in women who have difficulties conceiving (8.3)

FULL PRESCRIBING INFORMATION

WARNING: RISK OF SERIOUS CARDIOVASCULAR AND GASTROINTESTINAL EVENTS

Cardiovascular Thrombotic Events

- Nonsteroidal anti-inflammatory drugs (NSAIDs) cause an increased risk of serious cardiovascular thrombotic events, including myocardial infarction and stroke, which can be fatal. This risk may occur early in treatment and may increase with duration of use [see Warnings and Precautions (5.1)].
- Zybic™ is contraindicated in the setting of coronary artery bypass graft (CABG) surgery [see Contraindications (4) and Warnings and Precautions (5.1)].

Gastrointestinal Bleeding, Ulceration, and Perforation

- NSAIDs cause an increased risk of serious gastrointestinal (GI) adverse events including bleeding, ulceration, and perforation of the stomach or intestines, which can be fatal. These events can occur at any time during use and without warning symptoms. Elderly patients and patients with a prior history of peptic ulcer disease and/or GI bleeding are at greater risk for serious GI events [see Warnings and Precautions (5.2)].

1 INDICATIONS AND USAGE

1.1 Osteoarthritis (OA)

Zybic™ is indicated for relief of the signs and symptoms of osteoarthritis [see Clinical Studies (14.1)].

1.2 Rheumatoid Arthritis (RA)

Zybic™ is indicated for relief of the signs and symptoms of rheumatoid arthritis [see Clinical Studies (14.1)].

1.3 Juvenile Rheumatoid Arthritis (JRA) Pauciarticular and Polyarticular Course

Zybic™ is indicated for relief of the signs and symptoms of pauciarticular or polyarticular course Juvenile Rheumatoid Arthritis in patients 2 years of age and older [see Clinical Studies (14.2)].

2 DOSAGE AND ADMINISTRATION

2.1 General Dosing Instructions

Carefully consider the potential benefits and risks of Zybic™ and other treatment options before deciding to use Zybic™. Use the lowest effective dosage for the shortest duration consistent with individual patient treatment goals [see Warnings and Precautions (5)].

After observing the response to initial therapy with Zybic™, adjust the dose to suit an individual patient's needs.

In adults, the maximum recommended daily oral dose of Zybic™ is 15 mg regardless of formulation. In patients with hemodialysis, a maximum daily dosage of 7.5 mg is recommended [see Use in Specific Populations (8.7) and Clinical Pharmacology (12.3)].

Zybic™ 7.5 mg/5 mL or 15 mg/10 mL may be substituted for meloxicam tablets 7.5 mg or 15 mg, respectively.

Shake the oral suspension gently before using.

Zybic™ may be taken without regard to timing of meals.

2.2 Osteoarthritis

For the relief of the signs and symptoms of osteoarthritis the recommended starting and maintenance oral dose of Zybic™ is 7.5 mg once daily. Some patients may receive additional benefit by increasing the dose to 15 mg once daily.

2.3 Rheumatoid Arthritis

For the relief of the signs and symptoms of rheumatoid arthritis, the recommended starting and maintenance oral dose of Zybic™ is 7.5 mg once daily. Some patients may receive additional benefit by increasing the dose to 15 mg once daily.

2.4 Juvenile Rheumatoid Arthritis (JRA) Pauciarticular and Polyarticular Course

To improve dosing accuracy in smaller weight children, the use of the Zybic™ is recommended. Zybic™ is available in the strength of 7.5 mg/5 mL. For the treatment of juvenile rheumatoid arthritis, the recommended oral dose of Zybic™ is 0.125 mg/kg once daily up to a maximum of 7.5 mg. There was no additional benefit demonstrated by increasing the dose above 0.125 mg/kg once daily in these clinical trials.

Juvenile Rheumatoid Arthritis dosing using the oral suspension should be individualized based on the weight of the child:

0.125 mg/kg
Weight | Dose (1.5 mg/mL) | Delivered dose
12 kg (26 lb) | 1.0 mL | 1.5 mg
24 kg (54 lb) | 2.0 mL | 3.0 mg
36 kg (80 lb) | 3.0 mL | 4.5 mg
48 kg (106 lb) | 4.0 mL | 6.0 mg
≥60 kg (132 lb) | 5.0 mL | 7.5 mg

2.5 Renal Impairment

The use of Zybic™ in subjects with severe renal impairment is not recommended.

In patients on hemodialysis, the maximum dosage of Zybic™ is 7.5 mg per day [see Clinical Pharmacology (12.3)].

2.6 Non-Interchangeability with Other Formulations of Meloxicam

Zybic™ has not shown equivalent systemic exposure to other approved formulations of oral meloxicam.

Therefore, Zybic™ is not interchangeable with other formulations of oral meloxicam product even if the total milligram strength is the same. Do not substitute similar dose strengths of Zybic™ with other formulations of oral meloxicam product.

3 DOSAGE FORMS AND STRENGTHS

Zybic™:

- yellowish green tinged viscous suspension containing 7.5 mg meloxicam per 5 mL.

4 CONTRAINDICATIONS

Zybic™ is contraindicated in the following patients:

- Known hypersensitivity (e.g., anaphylactic reactions and serious skin reactions) to meloxicam or any components of the drug product [see Warnings and Precautions (5.7, 5.9)]
- History of asthma, urticaria, or other allergic-type reactions after taking aspirin or other NSAIDs. Severe, sometimes fatal, anaphylactic reactions to NSAIDs have been reported in such patients [see Warnings and Precautions (5.7, 5.8)]
- In the setting of coronary artery bypass graft (CABG) surgery [see Warnings and Precautions (5.1)]

5 WARNINGS AND PRECAUTIONS

5.1 Cardiovascular Thrombotic Events

Clinical trials of several COX-2 selective and nonselective NSAIDs of up to three years duration have shown an increased risk of serious cardiovascular (CV) thrombotic events, including myocardial infarction (MI) and stroke, which can be fatal. Based on available data, it is unclear that the risk for CV thrombotic events is similar for all NSAIDs. The relative increase in serious CV thrombotic events over baseline conferred by NSAID use appears to be similar in those with and without known CV disease or risk factors for CV disease. However, patients with known CV disease or risk factors had a higher absolute incidence of excess serious CV thrombotic events, due to their increased baseline rate. Some observational studies found that this increased risk of serious CV thrombotic events began as early as the first weeks of treatment. The increase in CV thrombotic risk has been observed most consistently at higher doses.

To minimize the potential risk for an adverse CV event in NSAID-treated patients, use the lowest effective dose for the shortest duration possible. Physicians and patients should remain alert for the development of such events, throughout the entire treatment course, even in the absence of previous CV symptoms. Patients should be informed about the symptoms of serious CV events and the steps to take if they occur.

There is no consistent evidence that concurrent use of aspirin mitigates the increased risk of serious CV thrombotic events associated with NSAID use. The concurrent use of aspirin and an NSAID, such as meloxicam, increases the risk of serious gastrointestinal (GI) events [see Warnings and Precautions (5.2)].

Status Post Coronary Artery Bypass Graft (CABG) Surgery

Two large, controlled clinical trials of a COX-2 selective NSAID for the treatment of pain in the first 10-14 days following CABG surgery found an increased incidence of myocardial infarction and stroke. NSAIDs are contraindicated in the setting of CABG [see Contraindications (4)].

Post-MI Patients

Observational studies conducted in the Danish National Registry have demonstrated that patients treated with NSAIDs in the post-MI period were at increased risk of reinfarction, CV-related death, and all-cause mortality beginning in the first week of treatment. In this same cohort, the incidence of death in the first year post-MI was 20 per 100 person years in NSAID-treated patients compared to 12 per 100 person years in non-NSAID exposed patients. Although the absolute rate of death declined somewhat after the first year post-MI, the increased relative risk of death in NSAID users persisted over at least the next four years of follow-up.

Avoid the use of Zybic™ in patients with a recent MI unless the benefits are expected to outweigh the risk of recurrent CV thrombotic events. If Zybic™ is used in patients with a recent MI, monitor patients for signs of cardiac ischemia.

5.2 Gastrointestinal Bleeding, Ulceration, and Perforation

NSAIDs, including meloxicam, can cause serious gastrointestinal (GI) adverse events including inflammation, bleeding, ulceration, and perforation of the esophagus, stomach, small intestine, or large intestine, which can be fatal. These serious adverse events can occur at any time, with or without warning symptoms, in patients treated with NSAIDs. Only one in five patients who develop a serious upper GI adverse event on NSAID therapy is symptomatic. Upper GI ulcers, gross bleeding, or perforation caused by NSAIDs occurred in approximately 1% of patients treated for 3-6 months, and in about 2-4% of patients treated for one year. However, even short-term NSAID therapy is not without risk.

Risk Factors for GI Bleeding, Ulceration, and Perforation

Patients with a prior history of peptic ulcer disease and/or GI bleeding who used NSAIDs had a greater than 10-fold increased risk for developing a GI bleed compared to patients without these risk factors. Other factors that increase the risk of GI bleeding in patients treated with NSAIDs include longer duration of NSAID therapy; concomitant use of oral corticosteroids, aspirin, anticoagulants, or selective serotonin reuptake inhibitors (SSRIs); smoking; use of alcohol; older age; and poor general health status. Most postmarketing reports of fatal GI events occurred in elderly or debilitated patients. Additionally, patients with advanced liver disease and/or coagulopathy are at increased risk for GI bleeding.

Strategies to Minimize the GI Risks in NSAID-treated patients:

- Use the lowest effective dosage for the shortest possible duration.
- Avoid administration of more than one NSAID at a time.
- Avoid use in patients at higher risk unless benefits are expected to outweigh the increased risk of bleeding. For such patients, as well as those with active GI bleeding, consider alternate therapies other than NSAIDs.
- Remain alert for signs and symptoms of GI ulceration and bleeding during NSAID therapy.
- If a serious GI adverse event is suspected, promptly initiate evaluation and treatment, and discontinue Zybic™ until a serious GI adverse event is ruled out.
- In the setting of concomitant use of low-dose aspirin for cardiac prophylaxis, monitor patients more closely for evidence of GI bleeding [see Drug Interactions (7)].

5.3 Hepatotoxicity

Elevations of ALT or AST (three or more times the upper limit of normal [ULN]) have been reported in approximately 1% of NSAID-treated patients in clinical trials. In addition, rare, sometimes fatal, cases of severe hepatic injury, including fulminant hepatitis, liver necrosis, and hepatic failure have been reported.

Elevations of ALT or AST (less than three times ULN) may occur in up to 15% of patients treated with NSAIDs including meloxicam.

Inform patients of the warning signs and symptoms of hepatotoxicity (e.g., nausea, fatigue, lethargy, diarrhea, pruritus, jaundice, right upper quadrant tenderness, and "flu-like" symptoms). If clinical signs and symptoms consistent with liver disease develop, or if systemic manifestations occur (e.g., eosinophilia, rash, etc.), discontinue Zybic™ immediately, and perform a clinical evaluation of the patient [see Use in Specific Populations (8.6) and Clinical Pharmacology (12.3)].

5.4 Hypertension

NSAIDs, including Zybic™, can lead to new onset or worsening of preexisting hypertension, either of which may contribute to the increased incidence of CV events. Patients taking angiotensin converting enzyme (ACE) inhibitors, thiazide diuretics, or loop diuretics may have impaired response to these therapies when taking NSAIDs [see Drug Interactions (7)].

Monitor blood pressure (BP) during the initiation of NSAID treatment and throughout the course of therapy.

5.5 Heart Failure and Edema

The Coxib and traditional NSAID Trialists' Collaboration meta-analysis of randomized controlled trials demonstrated an approximately two-fold increase in hospitalizations for heart failure in COX-2 selective-treated patients and nonselective NSAID-treated patients compared to placebo-treated patients. In a Danish National Registry study of patients with heart failure, NSAID use increased the risk of MI, hospitalization for heart failure, and death.

Additionally, fluid retention and edema have been observed in some patients treated with NSAIDs. Use of meloxicam may blunt the CV effects of several therapeutic agents used to treat these medical conditions (e.g., diuretics, ACE inhibitors, or angiotensin receptor blockers [ARBs]) [see Drug Interactions (7)].

Avoid the use of Zybic™ in patients with severe heart failure unless the benefits are expected to outweigh the risk of worsening heart failure. If Zybic™ is used in patients with severe heart failure, monitor patients for signs of worsening heart failure.

5.6 Renal Toxicity and Hyperkalemia

Renal Toxicity

Long-term administration of NSAIDs, including Zybic™, has resulted in renal papillary necrosis, renal insufficiency, acute renal failure, and other renal injury.

Renal toxicity has also been seen in patients in whom renal prostaglandins have a compensatory role in the maintenance of renal perfusion. In these patients, administration of an NSAID may cause a dose-dependent reduction in prostaglandin formation and, secondarily, in renal blood flow, which may precipitate overt renal decompensation. Patients at greatest risk of this reaction are those with impaired renal function, dehydration, hypovolemia, heart failure, liver dysfunction, those taking diuretics and ACE inhibitors or ARBs, and the elderly. Discontinuation of NSAID therapy is usually followed by recovery to the pretreatment state.

The renal effects of Zybic™ may hasten the progression of renal dysfunction in patients with preexisting renal disease. Because some Zybic™ metabolites are excreted by the kidney, monitor patients for signs of worsening renal function.

Correct volume status in dehydrated or hypovolemic patients prior to initiating Zybic™. Monitor renal function in patients with renal or hepatic impairment, heart failure, dehydration, or hypovolemia during use of Zybic™ [see Drug Interactions (7)].

No information is available from controlled clinical studies regarding the use of Zybic™ in patients with advanced renal disease. Avoid the use of Zybic™ in patients with advanced renal disease unless the benefits are expected to outweigh the risk of worsening renal function. If Zybic™ is used in patients with advanced renal disease, monitor patients for signs of worsening renal function [see Clinical Pharmacology (12.3)].

Hyperkalemia

Increases in serum potassium concentration, including hyperkalemia, have been reported with use of NSAIDs, even in some patients without renal impairment. In patients with normal renal function, these effects have been attributed to a hyporeninemic-hypoaldosteronism state.

5.7 Anaphylactic Reactions

Meloxicam has been associated with anaphylactic reactions in patients with and without known hypersensitivity to meloxicam and in patients with aspirin-sensitive asthma [see Contraindications (4) and Warnings and Precautions (5.8)].

Seek emergency help if an anaphylactic reaction occurs.

5.8 Exacerbation of Asthma Related to Aspirin Sensitivity

A subpopulation of patients with asthma may have aspirin-sensitive asthma which may include chronic rhinosinusitis complicated by nasal polyps; severe, potentially fatal bronchospasm; and/or intolerance to aspirin and other NSAIDs. Because cross-reactivity between aspirin and other NSAIDs has been reported in such aspirin-sensitive patients, Zybic™ is contraindicated in patients with this form of aspirin sensitivity [see Contraindications (4)]. When Zybic™ is used in patients with preexisting asthma (without known aspirin sensitivity), monitor patients for changes in the signs and symptoms of asthma.

5.9 Serious Skin Reactions

NSAIDs, including meloxicam, can cause serious skin adverse reactions such as exfoliative dermatitis, Stevens-Johnson Syndrome (SJS), and toxic epidermal necrolysis (TEN), which can be fatal. NSAIDs can also cause fixed drug eruption (FDE). FDE may present as a more severe variant known as generalized bullous fixed drug eruption (GBFDE), which can be life-threatening. These serious events may occur without warning. Inform patients about the signs and symptoms of serious skin reactions, and to discontinue the use of Zybic™ at the first appearance of skin rash or any other sign of hypersensitivity. Zybic™ is contraindicated in patients with previous serious skin reactions to NSAIDs [see Contraindications (4)].

5.10 Drug Reaction with Eosinophilia and Systemic Symptoms (DRESS)

Drug Reaction with Eosinophilia and Systemic Symptoms (DRESS) has been reported in patients taking NSAIDs such as Zybic™. Some of these events have been fatal or life-threatening. DRESS typically, although not exclusively, presents with fever, rash, lymphadenopathy, and/or facial swelling. Other clinical manifestations may include hepatitis, nephritis, hematological abnormalities, myocarditis, or myositis. Sometimes symptoms of DRESS may resemble an acute viral infection. Eosinophilia is often present. Because this disorder is variable in its presentation, other organ systems not noted here may be involved. It is important to note that early manifestations of hypersensitivity, such as fever or lymphadenopathy, may be present even though rash is not evident. If such signs or symptoms are present, discontinue Zybic™ and evaluate the patient immediately.

5.11 Fetal Toxicity

Premature Closure of Fetal Ductus Arteriosus

Avoid use of NSAIDs, including Zybic™, in pregnant women at about 30 weeks gestation and later. NSAIDs, including Zybic™, increase the risk of premature closure of the fetal ductus arteriosus at approximately this gestational age.

Oligohydramnios/Neonatal Renal Impairment

Use of NSAIDs, including Zybic™, at about 20 weeks gestation or later in pregnancy may cause fetal renal dysfunction leading to oligohydramnios and, in some cases, neonatal renal impairment. These adverse outcomes are seen, on average, after days to weeks of treatment, although oligohydramnios has been infrequently reported as soon as 48 hours after NSAID initiation.

Oligohydramnios is often, but not always, reversible with treatment discontinuation. Complications of prolonged oligohydramnios may, for example, include limb contractures and delayed lung maturation. In some postmarketing cases of impaired neonatal renal function, invasive procedures such as exchange transfusion or dialysis were required.

If NSAID treatment is necessary between about 20 weeks and 30 weeks gestation, limit Zybic™ use to the lowest effective dose and shortest duration possible. Consider ultrasound monitoring of amniotic fluid if Zybic™ treatment extends beyond 48 hours. Discontinue meloxicam oral suspension if oligohydramnios occurs and follow up according to clinical practice [see Use in Specific Populations (8.1)].

5.12 Hematologic Toxicity

Anemia has occurred in NSAID-treated patients. This may be due to occult or gross blood loss, fluid retention, or an incompletely described effect on erythropoiesis. If a patient treated with Zybic™ has any signs or symptoms of anemia, monitor hemoglobin or hematocrit.

NSAIDs, including Zybic™, may increase the risk of bleeding events. Co-morbid conditions such as coagulation disorders or concomitant use of warfarin, other anticoagulants, antiplatelet agents (e.g., aspirin), serotonin reuptake inhibitors (SSRIs) and serotonin norepinephrine reuptake inhibitors (SNRIs) may increase this risk. Monitor these patients for signs of bleeding [see Drug Interactions (7)].

5.13 Masking of Inflammation and Fever

The pharmacological activity of Zybic™ in reducing inflammation, and possibly fever, may diminish the utility of diagnostic signs in detecting infections.

5.14 Laboratory Monitoring

Because serious GI bleeding, hepatotoxicity, and renal injury can occur without warning symptoms or signs, consider monitoring patients on long-term NSAID treatment with a CBC and a chemistry profile periodically [see Warnings and Precautions (5.2, 5.3, 5.6)].

6 ADVERSE REACTIONS

The following adverse reactions are discussed in greater detail in other sections of the labeling:

- Cardiovascular Thrombotic Events [see Boxed Warning and Warnings and Precautions (5.1)]
- GI Bleeding, Ulceration, and Perforation [see Boxed Warning and Warnings and Precautions (5.2)]
- Hepatotoxicity [see Warnings and Precautions (5.3)]
- Hypertension [see Warnings and Precautions (5.4)]
- Heart Failure and Edema [see Warnings and Precautions (5.5)]
- Renal Toxicity and Hyperkalemia [see Warnings and Precautions (5.6)]
- Anaphylactic Reactions [see Warnings and Precautions (5.7)]
- Serious Skin Reactions [see Warnings and Precautions (5.9)]
- Hematologic Toxicity [see Warnings and Precautions (5.12)]

6.1 Clinical Trials Experience

Because clinical trials are conducted under widely varying conditions, adverse reaction rates observed in the clinical trials of a drug cannot be directly compared to rates in the clinical trials of another drug and may not reflect the rates observed in practice.

Adults

Osteoarthritis and Rheumatoid Arthritis

The meloxicam Phase 2/3 clinical trial database includes 10,122 OA patients and 1012 RA patients treated with meloxicam 7.5 mg/day, 3505 OA patients and 1351 RA patients treated with meloxicam 15 mg/day. Meloxicam at these doses was administered to 661 patients for at least 6 months and to 312 patients for at least one year. Approximately 10,500 of these patients were treated in ten placebo- and/or active-controlled osteoarthritis trials and 2363 of these patients were treated in ten placebo- and/or active-controlled rheumatoid arthritis trials. Gastrointestinal (GI) adverse events were the most frequently reported adverse events in all treatment groups across meloxicam trials.

A 12-week multicenter, double-blind, randomized trial was conducted in patients with osteoarthritis of the knee or hip to compare the efficacy and safety of meloxicam with placebo and with an active control. Two 12-week multicenter, double-blind, randomized trials were conducted in patients with rheumatoid arthritis to compare the efficacy and safety of meloxicam with placebo.

Table 1a depicts adverse events that occurred in ≥2% of the meloxicam treatment groups in a 12-week placebo-and active-controlled osteoarthritis trial.

Table 1b depicts adverse events that occurred in ≥2% of the meloxicam treatment groups in two 12-week placebo-controlled rheumatoid arthritis trials.

Table 1a Adverse Events (%) Occurring in ≥2% of Meloxicam Patients in a 12-Week Osteoarthritis Placebo-and Active-Controlled Trial
 | Placebo | Meloxicam 7.5 mg daily | Meloxicam 15 mg daily | Diclofenac 100 mg daily
No. of Patients | 157 | 154 | 156 | 153
Gastrointestinal | 17.2 | 20.1 | 17.3 | 28.1
Abdominal pain | 2.5 | 1.9 | 2.6 | 1.3
Diarrhea | 3.8 | 7.8 | 3.2 | 9.2
Dyspepsia | 4.5 | 4.5 | 4.5 | 6.5
Flatulence | 4.5 | 3.2 | 3.2 | 3.9
Nausea | 3.2 | 3.9 | 3.8 | 7.2
Body as a Whole
Accident household | 1.9 | 4.5 | 3.2 | 2.6
Edema [WHO preferred terms edema, edema dependent, edema peripheral, and edema legs combined] | 2.5 | 1.9 | 4.5 | 3.3
Fall | 0.6 | 2.6 | 0.0 | 1.3
Influenza-like symptoms | 5.1 | 4.5 | 5.8 | 2.6
Central and Peripheral Nervous System
Dizziness | 3.2 | 2.6 | 3.8 | 2.0
Headache | 10.2 | 7.8 | 8.3 | 5.9
Respiratory
Pharyngitis | 1.3 | 0.6 | 3.2 | 1.3
Upper respiratory tract infection | 1.9 | 3.2 | 1.9 | 3.3
Skin
Rash [WHO preferred terms rash, rash erythematous, and rash maculo-papular combined.] | 2.5 | 2.6 | 0.6 | 2.0

Table 1b Adverse Events (%) Occurring in ≥2% of Meloxicam Patients in Two 12-Week Rheumatoid Arthritis Placebo-Controlled Trials
 | Placebo | Meloxicam 7.5 mg daily | Meloxicam 15 mg daily
No. of Patients | 469 | 481 | 477
Gastrointestinal Disorders | 14.1 | 18.9 | 16.8
Abdominal pain NOS [MedDRA preferred term: nausea, abdominal pain NOS, influenza-like illness, headaches NOS, and rash NOS] | 0.6 | 2.9 | 2.3
Dyspeptic signs and symptoms [MedDRA high level term (preferred terms): dyspeptic signs and symptoms (dyspepsia, dyspepsia aggravated, eructation, gastrointestinal irritation), upper respiratory tract infections-pathogen unspecified (laryngitis NOS, pharyngitis NOS, sinusitis NOS), joint related signs and symptoms (arthralgia, arthralgia aggravated, joint crepitation, joint effusion, joint swelling)] | 3.8 | 5.8 | 4.0
Nausea | 2.6 | 3.3 | 3.8
General Disorders and Administration Site Conditions
Influenza-like illness | 2.1 | 2.9 | 2.3
Infection and Infestations
Upper respiratory tract infectionspathogen class unspecified | 4.1 | 7.0 | 6.5
Musculoskeletal and Connective Tissue Disorders
Joint related signs and symptoms | 1.9 | 1.5 | 2.3
Nervous System Disorders
Headaches NOS | 6.4 | 6.4 | 5.5
Skin and Subcutaneous Tissue Disorders
Rash NOS | 1.7 | 1.0 | 2.1

The adverse events that occurred with Zybic™ in ≥2% of patients treated short-term (4 to 6 weeks) and long-term (6 months) in active-controlled osteoarthritis trials are presented in Table 2.

Table 2 Adverse Events (%) Occurring in ≥2% of Meloxicam Patients in 4 to 6 Weeks and 6 Month Active-Controlled Osteoarthritis Trials
 | 4 to 6 Weeks Controlled Trials |  | 6 Month Controlled Trials
 | Meloxicam 7.5 mg daily | Meloxicam 15 mg daily | Meloxicam 7.5 mg daily | Meloxicam 15 mg daily
No. of Patients | 8955 | 256 | 169 | 306
Gastrointestinal | 11.8 | 18.0 | 26.6 | 24.2
Abdominal pain | 2.7 | 2.3 | 4.7 | 2.9
Constipation | 0.8 | 1.2 | 1.8 | 2.6
Diarrhea | 1.9 | 2.7 | 5.9 | 2.6
Dyspepsia | 3.8 | 7.4 | 8.9 | 9.5
Flatulence | 0.5 | 0.4 | 3.0 | 2.6
Nausea | 2.4 | 4.7 | 4.7 | 7.2
Vomiting | 0.6 | 0.8 | 1.8 | 2.6
Body as a Whole
Accident household | 0.0 | 0.0 | 0.6 | 2.9
Edema [WHO preferred terms edema, edema dependent, edema peripheral, and edema legs combined] | 0.6 | 2.0 | 2.4 | 1.6
Pain | 0.9 | 2.0 | 3.6 | 5.2
Central and Peripheral Nervous System
Dizziness | 1.1 | 1.6 | 2.4 | 2.6
Headache | 2.4 | 2.7 | 3.6 | 2.6
Hematologic
Anemia | 0.1 | 0.0 | 4.1 | 2.9
Musculoskeletal
Arthralgia | 0.5 | 0.0 | 5.3 | 1.3
Back pain | 0.5 | 0.4 | 3.0 | 0.7
Psychiatric
Insomnia | 0.4 | 0.0 | 3.6 | 1.6
Respiratory
Coughing | 0.2 | 0.8 | 2.4 | 1.0
Upper respiratory tract infection | 0.2 | 0.0 | 8.3 | 7.5
Skin
Pruritus | 0.4 | 1.2 | 2.4 | 0.0
Rash [WHO preferred terms rash, rash erythematous, and rash maculo-papular combined] | 0.3 | 1.2 | 3.0 | 1.3
Urinary
Micturition frequency | 0.1 | 0.4 | 2.4 | 1.3
Urinary tract infection | 0.3 | 0.4 | 4.7 | 6.9

Higher doses of meloxicam (22.5 mg and greater) have been associated with an increased risk of serious GI events; therefore, the daily dose of Zybic™ should not exceed 15 mg.

Pediatrics

Pauciarticular and Polyarticular Course Juvenile Rheumatoid Arthritis (JRA)

Three hundred and eighty-seven patients with pauciarticular and polyarticular course JRA were exposed to meloxicam with doses ranging from 0.125 to 0.375 mg/kg per day in three clinical trials. These studies consisted of two 12-week multicenter, double-blind, randomized trials (one with a 12-week open-label extension and one with a 40-week extension) and one 1-year open-label PK study. The adverse events observed in these pediatric studies with meloxicam were similar in nature to the adult clinical trial experience, although there were differences in frequency. In particular, the following most common adverse events, abdominal pain, vomiting, diarrhea, headache, and pyrexia, were more common in the pediatric than in the adult trials. Rash was reported in seven (<2%) patients receiving meloxicam. No unexpected adverse events were identified during the course of the trials. The adverse events did not demonstrate an age or gender-specific subgroup effect.

The following is a list of adverse drug reactions occurring in <2% of patients receiving meloxicam in clinical trials involving approximately 16,200 patients.

Body as a Whole | allergic reaction, face edema, fatigue, fever, hot flushes, malaise, syncope, weight decrease, weight increase angina pectoris, cardiac failure, hypertension, hypotension, myocardial infarction, vasculitis
Cardiovascular | allergic reaction, face edema, fatigue, fever, hot flushes, malaise, syncope, weight decrease, weight increase angina pectoris, cardiac failure, hypertension, hypotension, myocardial infarction, vasculitis
Central and Peripheral Nervous System | convulsions, paresthesia, tremor, vertigo
Gastrointestinal | colitis, dry mouth, duodenal ulcer, eructation, esophagitis, gastric ulcer, gastritis, gastroesophageal reflux, gastrointestinal hemorrhage, hematemesis, hemorrhagic duodenal ulcer, hemorrhagic gastric ulcer, intestinal perforation, melena, pancreatitis, perforated duodenal ulcer, perforated gastric ulcer, stomatitis ulcerative
Heart Rate and Rhythm | arrhythmia, palpitation, tachycardia
Hematologic | leukopenia, purpura, thrombocytopenia
Liver and Biliary System | ALT increased, AST increased, bilirubinemia, GGT increased, hepatitis
Metabolic and Nutritional | dehydration
Psychiatric | abnormal dreaming, anxiety, appetite increased, confusion, depression, nervousness, somnolence
Respiratory | asthma, bronchospasm, dyspnea
Skin and Appendages | alopecia, angioedema, bullous eruption, photosensitivity reaction, pruritus, sweating increased, urticaria
Special Senses | abnormal vision, conjunctivitis, taste perversion, tinnitus
Urinary System | albuminuria, BUN increased, creatinine increased, hematuria, renal failure

6.2 Postmarketing Experience

The following adverse reactions have been identified during post approval use of meloxicam. Because these reactions are reported voluntarily from a population of uncertain size, it is not always possible to reliably estimate their frequency or establish a causal relationship to drug exposure. Decisions about whether to include an adverse event from spontaneous reports in labeling are typically based on one or more of the following factors: (1) seriousness of the event, (2) number of reports, or (3) strength of causal relationship to the drug. Adverse reactions reported in worldwide post marketing experience or the literature include: acute urinary retention; agranulocytosis; alterations in mood (such as mood elevation); anaphylactoid reactions including shock; erythema multiforme; exfoliative dermatitis; interstitial nephritis; jaundice; liver failure; Stevens-Johnson syndrome; fixed drug eruption (FDE); toxic epidermal necrolysis, and infertility female.

7 DRUG INTERACTIONS

See Table 3 for clinically significant drug interactions with meloxicam. See also Warnings and Precautions (5.2, 5.6, 5.12) and Clinical Pharmacology (12.3).

Table 3 Clinically Significant Drug Interactions with Meloxicam

Drugs that Interfere with Hemostasis

Clinical Impact:

- Meloxicam and anticoagulants such as warfarin have a synergistic effect on bleeding. The concomitant use of meloxicam and anticoagulants have an increased risk of serious bleeding compared to the use of either drug alone.
- Serotonin release by platelets plays an important role in hemostasis. Case-control and cohort epidemiological studies showed that concomitant use of drugs that interfere with serotonin reuptake and an NSAID may potentiate the risk of bleeding more than an NSAID alone.

Intervention:
Monitor patients with concomitant use of Zybic™ with anticoagulants (e.g., warfarin), antiplatelet agents (e.g., aspirin), selective serotonin reuptake inhibitors (SSRIs), and serotonin norepinephrine reuptake inhibitors (SNRIs) for signs of bleeding [see Warnings and Precautions (5.12)].

Aspirin

Clinical Impact:
Controlled clinical studies showed that the concomitant use of NSAIDs and analgesic doses of aspirin does not produce any greater therapeutic effect than the use of NSAIDs alone. In a clinical study, the concomitant use of an NSAID and aspirin was associated with a significantly increased incidence of GI adverse reactions as compared to use of the NSAID alone [see Warnings and Precautions (5.2)].

Intervention:
Concomitant use of Zybic™ and low dose aspirin or analgesic doses of aspirin is not generally recommended because of the increased risk of bleeding [see Warnings and Precautions (5.12)].
Zybic™ is not a substitute for low dose aspirin for cardiovascular protection.

ACE Inhibitors, Angiotensin Receptor Blockers, or Beta-Blockers

Clinical Impact:

- NSAIDs may diminish the antihypertensive effect of angiotensin converting enzyme (ACE) inhibitors, angiotensin receptor blockers (ARBs), or beta-blockers (including propranolol).
- In patients who are elderly, volume-depleted (including those on diuretic therapy), or have renal impairment, co-administration of an NSAID with ACE inhibitors or ARBs may result in deterioration of renal function, including possible acute renal failure. These effects are usually reversible.

Intervention:

- During concomitant use of Zybic™ and ACE inhibitors, ARBs, or beta-blockers, monitor blood pressure to ensure that the desired blood pressure is obtained.
- During concomitant use of Zybic™ and ACE inhibitors or ARBs in patients who are elderly, volume-depleted, or have impaired renal function, monitor for signs of worsening renal function [see Warnings and Precautions (5.6)].
- When these drugs are administered concomitantly, patients should be adequately hydrated. Assess renal function at the beginning of the concomitant treatment and periodically thereafter.

Diuretics

Clinical Impact:
Clinical studies, as well as post-marketing observations, showed that NSAIDs reduced the natriuretic effect of loop diuretics (e.g., furosemide) and thiazide diuretics in some patients. This effect has been attributed to the NSAID inhibition of renal prostaglandin synthesis. However, studies with furosemide agents and meloxicam have not demonstrated a reduction in natriuretic effect. Furosemide single and multiple dose pharmacodynamics and pharmacokinetics are not affected by multiple doses of meloxicam.

Intervention:
During concomitant use of Zybic™ with diuretics, observe patients for signs of worsening renal function, in addition to assuring diuretic efficacy including antihypertensive effects [see Warnings and Precautions (5.6)].

Lithium

Clinical Impact:
NSAIDs have produced elevations in plasma lithium levels and reductions in renal lithium clearance. The mean minimum lithium concentration increased 15%, and the renal clearance decreased by approximately 20%.
This effect has been attributed to NSAID inhibition of renal prostaglandin synthesis [see Clinical Pharmacology (12.3)].

Intervention:
During concomitant use of Zybic™ and lithium, monitor patients for signs of lithium toxicity.

Methotrexate

Clinical Impact:
Concomitant use of NSAIDs and methotrexate may increase the risk of methotrexate toxicity (e.g., neutropenia, thrombocytopenia, renal dysfunction).

Intervention:
During concomitant use of Zybic™ and methotrexate, monitor patients for methotrexate toxicity.

Cyclosporine

Clinical Impact:
Concomitant use of meloxicam and cyclosporine may increase cyclosporine's nephrotoxicity.

Intervention:
During concomitant use of Zybic™ and cyclosporine, monitor patients for signs of worsening renal function.

NSAIDs and Salicylates

Clinical Impact:
Concomitant use of meloxicam with other NSAIDs or salicylates (e.g., diflunisal, salsalate) increases the risk of GI toxicity, with little or no increase in efficacy [see Warnings and Precautions (5.2)].

Intervention:
The concomitant use of Zybic™ with other NSAIDs or salicylates is not recommended.

Pemetrexed

Clinical Impact:
Concomitant use of meloxicam and pemetrexed may increase the risk of pemetrexed-associated myelosuppression, renal, and GI toxicity (see the pemetrexed prescribing information).

Intervention:
During concomitant use of Zybic™ and pemetrexed, in patients with renal impairment whose creatinine clearance ranges from 45 to 79 mL/min, monitor for myelosuppression, renal and GI toxicity.
Patients taking meloxicam should interrupt dosing for at least five days before, the day of, and two days following pemetrexed administration.
In patients with creatinine clearance below 45 mL/min, the concomitant administration of meloxicam with pemetrexed is not recommended.

Sodium Polystyrene Sulfonate

Clinical Impact:
Cases of intestinal necrosis (possibly fatal) have been described in patients who received concomitant sorbitol and sodium polystyrene sulfonate. Due to the presence of sorbitol in Zybic™, use with sodium polystyrene sulfonate is not recommended.

Intervention:
The concomitant use of Zybic™ with sodium polystyrene sulfonate is not recommended.

8 USE IN SPECIFIC POPULATIONS

8.1 Pregnancy

Risk Summary

Use of NSAIDs, including Zybic™, can cause premature closure of the fetal ductus arteriosus and fetal renal dysfunction leading to oligohydramnios and, in some cases, neonatal renal impairment. Because of these risks, limit dose and duration of Zybic™ use between about 20 and 30 weeks of gestation, and avoid Zybic™ use at about 30 weeks of gestation and later in pregnancy (see Clinical Considerations, Data).

Premature Closure of Fetal Ductus Arteriosus

Use of NSAIDs, including Zybic™, at about 30 weeks gestation or later in pregnancy increases the risk of premature closure of the fetal ductus arteriosus.

Oligohydramnios/Neonatal Renal Impairment

Use of NSAIDs at about 20 weeks gestation or later in pregnancy has been associated with cases of fetal renal dysfunction leading to oligohydramnios, and in some cases, neonatal renal impairment.

Data from observational studies regarding other potential embryofetal risks of NSAID use in women in the first or second trimesters of pregnancy are inconclusive. In animal reproduction studies, embryofetal death was observed in rats and rabbits treated during the period of organogenesis with meloxicam at oral doses equivalent to 0.65- and 6.5-times the maximum recommended human dose (MRHD) of Zybic™. Increased incidence of septal heart defects were observed in rabbits treated throughout embryogenesis with meloxicam at an oral dose equivalent to 78-times the MRHD. In pre- and post-natal reproduction studies, there was an increased incidence of dystocia, delayed parturition, and decreased offspring survival at 0.08-times MRHD of meloxicam. No teratogenic effects were observed in rats and rabbits treated with meloxicam during organogenesis at an oral dose equivalent to 2.6 and 26-times the MRHD [see Data].

Based on animal data, prostaglandins have been shown to have an important role in endometrial vascular permeability, blastocyst implantation, and decidualization. In animal studies, administration of prostaglandin synthesis inhibitors such as meloxicam, resulted in increased pre- and post-implantation loss. Prostaglandins also have been shown to have an important role in fetal kidney development. In published animal studies, prostaglandin synthesis inhibitors have been reported to impair kidney development when administered at clinically relevant doses.

The estimated background risk of major birth defects and miscarriage for the indicated population(s) is unknown. All pregnancies have a background risk of birth defect, loss, or other adverse outcomes. In the U.S. general population, the estimated background risk of major birth defects and miscarriage in clinically recognized pregnancies is 2% to 4% and 15% to 20%, respectively.

Clinical Considerations

Fetal/Neonatal Adverse Reactions

Premature Closure of Fetal Ductus Arteriosus:

Avoid use of NSAIDs in women at about 30 weeks gestation and later in pregnancy, because NSAIDs, including Zybic™, can cause premature closure of the fetal ductus arteriosus (see Data).

Oligohydramnios/Neonatal Renal Impairment:

If an NSAID is necessary at about 20 weeks gestation or later in pregnancy, limit the use to the lowest effective dose and shortest duration possible. If Zybic™ treatment extends beyond 48 hours, consider monitoring with ultrasound for oligohydramnios. If oligohydramnios occurs, discontinue Zybic™ and follow up according to clinical practice (see Data).

Labor or Delivery

There are no studies on the effects of Zybic™ during labor or delivery. In animal studies, NSAIDs, including meloxicam, inhibit prostaglandin synthesis, cause delayed parturition, and increase the incidence of stillbirth.

Data

Human Data

Premature Closure of Fetal Ductus Arteriosus:

Published literature reports that the use of NSAIDs at about 30 weeks of gestation and later in pregnancy may cause premature closure of the fetal ductus arteriosus.

Oligohydramnios/Neonatal Renal Impairment:

Published studies and postmarketing reports describe maternal NSAID use at about 20 weeks gestation or later in pregnancy associated with fetal renal dysfunction leading to oligohydramnios, and in some cases, neonatal renal impairment. These adverse outcomes are seen, on average, after days to weeks of treatment, although oligohydramnios has been infrequently reported as soon as 48 hours after NSAID initiation. In many cases, but not all, the decrease in amniotic fluid was transient and reversible with cessation of the drug. There have been a limited number of case reports of maternal NSAID use and neonatal renal dysfunction without oligohydramnios, some of which were irreversible. Some cases of neonatal renal dysfunction required treatment with invasive procedures, such as exchange transfusion or dialysis.

Methodological limitations of these postmarketing studies and reports include lack of a control group; limited information regarding dose, duration, and timing of drug exposure; and concomitant use of other medications. These limitations preclude establishing a reliable estimate of the risk of adverse fetal and neonatal outcomes with maternal NSAID use. Because the published safety data on neonatal outcomes involved mostly preterm infants, the generalizability of certain reported risks to the fullterm infant exposed to NSAIDs through maternal use is uncertain.

Animal Data

Meloxicam was not teratogenic when administered to pregnant rats during fetal organogenesis at oral doses up to 4 mg/kg/day (2.6-fold greater than the MRHD of 15 mg of meloxicam based on BSA comparison). Administration of meloxicam to pregnant rabbits throughout embryogenesis produced an increased incidence of septal defects of the heart at an oral dose of 60 mg/kg/day (78-fold greater than the MRHD based on BSA comparison). The no effect level was 20 mg/kg/day (26-fold greater than the MRHD based on BSA conversion). In rats and rabbits, embryolethality occurred at oral meloxicam doses of 1 mg/kg/day and 5 mg/ kg/day, respectively (0.65- and 6.5-fold greater, respectively, than the MRHD based on BSA comparison) when administered throughout organogenesis.

Oral administration of meloxicam to pregnant rats during late gestation through lactation increased the incidence of dystocia, delayed parturition, and decreased offspring survival at meloxicam doses of 0.125 mg/ kg/day or greater (0.08-times MRHD based on BSA comparison).

8.2 Lactation

Risk Summary

There are no human data available on whether meloxicam is present in human milk, or on the effects on breastfed infants, or on milk production. The developmental and health benefits of breastfeeding should be considered along with the mother's clinical need for Zybic™ and any potential adverse effects on the breastfed infant from the Zybic™ or from the underlying maternal condition.

Data

Animal Data

Meloxicam was present in the milk of lactating rats at concentrations higher than those in plasma.

8.3 Females and Males of Reproductive Potential

Infertility

Females

Based on the mechanism of action, the use of prostaglandin-mediated NSAIDs, including Zybic™, may delay or prevent rupture of ovarian follicles, which has been associated with reversible infertility in some women. Published animal studies have shown that administration of prostaglandin synthesis inhibitors has the potential to disrupt prostaglandin-mediated follicular rupture required for ovulation. Small studies in women treated with NSAIDs have also shown a reversible delay in ovulation. Consider withdrawal of NSAIDs, including Zybic™, in women who have difficulties conceiving or who are undergoing investigation of infertility.

8.4 Pediatric Use

The safety and effectiveness of meloxicam in pediatric JRA patients from 2 to 17 years of age has been evaluated in three clinical trials [see Dosage and Administration (2.3), Adverse Reactions (6.1) and Clinical Studies (14.2)].

8.5 Geriatric Use

Elderly patients, compared to younger patients, are at greater risk for NSAID-associated serious cardiovascular, gastrointestinal, and/or renal adverse reactions. If the anticipated benefit for the elderly patient outweighs these potential risks, start dosing at the low end of the dosing range, and monitor patients for adverse effects [see Warnings and Precautions (5.1, 5.2, 5.3, 5.6, 5.14)].

8.6 Hepatic Impairment

No dose adjustment is necessary in patients with mild to moderate hepatic impairment. Patients with severe hepatic impairment have not been adequately studied. Since meloxicam is significantly metabolized in the liver and hepatotoxicity may occur, use meloxicam with caution in patients with hepatic impairment [see Warnings and Precautions (5.3) and Clinical Pharmacology (12.3)].

8.7 Renal Impairment

No dose adjustment is necessary in patients with mild to moderate renal impairment. Patients with severe renal impairment have not been studied. The use of Zybic™ in subjects with severe renal impairment is not recommended. In patients on hemodialysis, meloxicam should not exceed 7.5 mg per day. Meloxicam is not dialyzable [see Dosage and Administration (2.1) and Clinical Pharmacology (12.3)].

10 OVERDOSAGE

Symptoms following acute NSAID overdosages have been typically limited to lethargy, drowsiness, nausea, vomiting, and epigastric pain, which have been generally reversible with supportive care. Gastrointestinal bleeding has occurred. Hypertension, acute renal failure, respiratory depression, and coma have occurred, but were rare [see Warnings and Precautions (5.1, 5.2, 5.4, 5.6)].

Manage patients with symptomatic and supportive care following an NSAID overdosage. There are no specific antidotes. Consider emesis and/or activated charcoal (60 to 100 grams in adults, 1 to 2 grams per kg of body weight in pediatric patients) and/or osmotic cathartic in symptomatic patients seen within four hours of ingestion or in patients with a large overdosage (5 to 10 times the recommended dosage). Forced diuresis, alkalinization of urine, hemodialysis, or hemoperfusion may not be useful due to high protein binding.

There is limited experience with meloxicam overdosage. Cholestyramine is known to accelerate the clearance of meloxicam. Accelerated removal of meloxicam by 4 g oral doses of cholestyramine given three times a day was demonstrated in a clinical trial. Administration of cholestyramine may be useful following an overdosage.

For additional information about overdosage treatment, call a poison control center (1-800-222-1222).

11 DESCRIPTION

Zybic™, USP is a nonsteroidal anti-inflammatory drug (NSAID). Each bottle of Zybic™ contains 7.5 mg meloxicam per 5 mL. Meloxicam is chemically designated as 4-hydroxy-2-methyl-N-(5-methyl-2-thiazolyl)- 2H-1,2-benzothiazine-3-carboxamide-1,1-dioxide. The molecular weight is 351.4. Its empirical formula is C14 H13 N3O4 S2 and it has the following structural formula:

Meloxicam, is a pastel yellow solid, practically insoluble in water, with higher solubility observed in strong acids and bases. It is very slightly soluble in methanol. Meloxicam has an apparent partition coefficient (log P) app = 0.1 in n-octanol/buffer pH 7.4. Meloxicam has pKa values of 1.1 and 4.2.

Meloxicam is available as an oral suspension containing 7.5 mg meloxicam per 5 mL.

The inactive ingredients in Zybic™ include colloidal silicon dioxide, hydroxyethylcellulose, sorbitol, glycerol, xylitol, monobasic sodium phosphate (dihydrate), saccharin sodium, sodium benzoate, citric acid (monohydrate), raspberry flavor, and purified water.

12 CLINICAL PHARMACOLOGY

12.1 Mechanism of Action

Meloxicam has analgesic, anti-inflammatory, and antipyretic properties.

The mechanism of action of Zybic™, like that of other NSAIDs, is not completely understood but involves inhibition of cyclooxygenase (COX-1 and COX-2).

Meloxicam is a potent inhibitor of prostaglandin synthesis in vitro. Meloxicam concentrations reached during therapy have produced in vivo effects. Prostaglandins sensitize afferent nerves and potentiate the action of bradykinin in inducing pain in animal models. Prostaglandins are mediators of inflammation. Because meloxicam is an inhibitor of prostaglandin synthesis, its mode of action may be due to a decrease of prostaglandins in peripheral tissues.

12.3 Pharmacokinetics

Absorption

The absolute bioavailability of meloxicam capsules was 89% following a single oral dose of 30 mg compared with 30 mg IV bolus injection. Following single intravenous doses, dose-proportional pharmacokinetics were shown in the range of 5 mg to 60 mg. After multiple oral doses the pharmacokinetics of meloxicam capsules were dose-proportional over the range of 7.5 mg to 15 mg. Mean Cmax was achieved within four to five hours after a 7.5 mg meloxicam tablet was taken under fasted conditions, indicating a prolonged drug absorption. With multiple dosing, steady-state concentrations were reached by Day 5. A second meloxicam concentration peak occurs around 12 to 14 hours post-dose suggesting biliary recycling.

Zybic™ doses of 7.5 mg/5 mL and 15 mg/10 mL have been found to be bioequivalent to meloxicam 7.5 mg and 15 mg capsules, respectively. Meloxicam capsules have been shown to be bioequivalent to meloxicam tablets.

Table 4 Single Dose and Steady-State Pharmacokinetic Parameters for Oral 7.5 mg and 15 mg Meloxicam (Mean and % CV) [The parameter values in the table are from various studies]
 |  | Steady State |  |  | Single Dose
Pharmacokinetic |  | Healthy male Parameters | Elderly males adults | Elderly females | Renal failure | Hepatic insufficiency
(% CV) |  | (Fed) [not under high fat conditions] | (Fed) | (Fed) | (Fasted) | (Fasted)
 |  | 7.5 mg [meloxicam tablets] tablets | 15 mg capsules | 15 mg capsules | 15 mg capsules | 15 mg capsules
N |  | 18 | 5 | 8 | 12 | 12
Cmax | [μg/mL] | 1.05 (20) | 2.3 (59) | 3.2 (24) | 0.59 (36) | 0.84 (29)
tmax | [h] | 4.9 (8) | 5 (12) | 6 (27) | 4 (65) | 10 (87)
t1/2 | [h] | 20.1 (29) | 21 (34) | 24 (34) | 18 (46) | 16 (29)
CL/f | [mL/min] | 8.8 (29) | 9.9 (76) | 5.1 (22) | 19 (43) | 11 (44)
V z/f [Vz /f =Dose/(AUC∙Kel)] | [L] | 14.7 (32) | 15 (42) | 10 (30) | 26 (44) | 14 (29)

Food and Antacid Effects

Administration of meloxicam capsules following a high fat breakfast (75 g of fat) resulted in mean peak drug levels (i.e., Cmax) being increased by approximately 22% while the extent of absorption (AUC) was unchanged. The time to maximum concentration (Tmax) was achieved between 5 and 6 hours. In comparison, neither the AUC nor the Cmax values for meloxicam suspension were affected following a similar high fat meal, while mean Tmax values were increased to approximately 7 hours. No pharmacokinetic interaction was detected with concomitant administration of antacids. Based on these results, Zybic™ can be administered without regard to timing of meals or concomitant administration of antacids.

Distribution

The mean volume of distribution (Vss) of meloxicam is approximately 10 L. Meloxicam is ~99.4% bound to human plasma proteins (primarily albumin) within the therapeutic dose range. The fraction of protein binding is independent of drug concentration, over the clinically relevant concentration range, but decreases to ~99% in patients with renal disease. Meloxicam penetration into human red blood cells, after oral dosing, is less than 10%. Following a radiolabeled dose, over 90% of the radioactivity detected in the plasma was present as unchanged meloxicam.

Meloxicam concentrations in synovial fluid, after a single oral dose, range from 40% to 50% of those in plasma. The free fraction in synovial fluid is 2.5 times higher than in plasma, due to the lower albumin content in synovial fluid as compared to plasma. The significance of this penetration is unknown.

Elimination

Metabolism

Meloxicam is extensively metabolized in the liver. Meloxicam metabolites include 5'-carboxy meloxicam (60% of dose), from P-450 mediated metabolism formed by oxidation of an intermediate metabolite 5'-hydroxymethyl meloxicam which is also excreted to a lesser extent (9% of dose). In vitro studies indicate that CYP2C9 (cytochrome P450 metabolizing enzyme) plays an important role in this metabolic pathway with a minor contribution of the CYP3A4 isozyme. Patients' peroxidase activity is probably responsible for the other two metabolites which account for 16% and 4% of the administered dose, respectively. All the four metabolites are not known to have any in vivo pharmacological activity.

Excretion

Meloxicam excretion is predominantly in the form of metabolites, and occurs to equal extents in the urine and feces. Only traces of the unchanged parent compound are excreted in the urine (0.2%) and feces (1.6%). The extent of the urinary excretion was confirmed for unlabeled multiple 7.5 mg doses: 0.5%, 6%, and 13% of the dose were found in urine in the form of meloxicam, and the 5'-hydroxymethyl and 5'-carboxy metabolites, respectively. There is significant biliary and/or enteral secretion of the drug. This was demonstrated when oral administration of cholestyramine following a single IV dose of meloxicam decreased the AUC of meloxicam by 50%.

The mean elimination half-life (t1/2) ranges from 15 hours to 20 hours. The elimination half-life is constant across dose levels indicating linear metabolism within the therapeutic dose range. Plasma clearance ranges from 7 to 9 mL/min.

Specific Populations

Pediatric

After single (0.25 mg/kg) dose administration and after achieving steady state (0.375 mg/kg/day), there was a general trend of approximately 30% lower exposure in younger patients (2 to 6 years old) as compared to the older patients (7 to 16 years old). The older patients had meloxicam exposures similar (single dose) or slightly reduced (steady state) to those in the adult patients, when using AUC values normalized to a dose of 0.25 mg/ kg [see Dosage and Administration (2.4)]. The meloxicam mean (SD) elimination half-life was 15.2 (10.1) and 13.0 hours (3.0) for the 2 to 6 year old patients, and 7 to 16 year old patients, respectively.

In a covariate analysis, utilizing population pharmacokinetics body-weight, but not age, was the single predictive covariate for differences in the meloxicam apparent oral plasma clearance. The body-weight normalized apparent oral clearance values were adequate predictors of meloxicam exposure in pediatric patients.

The pharmacokinetics of Zybic™ in pediatric patients under 2 years of age have not been investigated.

Geriatric

Elderly males (≥65 years of age) exhibited meloxicam plasma concentrations and steady-state pharmacokinetics similar to young males. Elderly females (≥65 years of age) had a 47% higher AUCss and 32% higher Cmax,ss as compared to younger females (≤55 years of age) after body weight normalization. Despite the increased total concentrations in the elderly females, the adverse event profile was comparable for both elderly patient populations. A smaller free fraction was found in elderly female patients in comparison to elderly male patients.

Sex

Young females exhibited slightly lower plasma concentrations relative to young males. After single doses of 7.5 mg meloxicam, the mean elimination half-life was 19.5 hours for the female group as compared to 23.4 hours for the male group. At steady state, the data were similar (17.9 hours vs 21.4 hours). This pharmacokinetic difference due to gender is likely to be of little clinical importance. There was linearity of pharmacokinetics and no appreciable difference in the Cmax or Tmax across genders.

Hepatic Impairment

Following a single 15 mg dose of meloxicam there was no marked difference in plasma concentrations in patients with mild (Child-Pugh Class I) or moderate (Child-Pugh Class II) hepatic impairment compared to healthy volunteers. Protein binding of meloxicam was not affected by hepatic impairment. No dosage adjustment is necessary in patients with mild to moderate hepatic impairment. Patients with severe hepatic impairment (Child-Pugh Class III) have not been adequately studied [see Warnings and Precautions (5.3) and Use in Specific Populations (8.6)].

Renal Impairment

Meloxicam pharmacokinetics have been investigated in subjects with mild and moderate renal impairment. Total drug plasma concentrations of meloxicam decreased and total clearance of meloxicam increased with the degree of renal impairment while free AUC values were similar in all groups. The higher meloxicam clearance in subjects with renal impairment may be due to increased fraction of unbound meloxicam which is available for hepatic metabolism and subsequent excretion. No dosage adjustment is necessary in patients with mild to moderate renal impairment. Patients with severe renal impairment have not been adequately studied. The use of Zybic™ in subjects with severe renal impairment is not recommended [see Dosage and Administration (2.5), Warnings and Precautions (5.6) and Use in Specific Populations (8.7)].

Hemodialysis

Following a single dose of meloxicam, the free Cmax plasma concentrations were higher in patients with renal failure on chronic hemodialysis (1% free fraction) in comparison to healthy volunteers (0.3% free fraction). Hemodialysis did not lower the total drug concentration in plasma; therefore, additional doses are not necessary after hemodialysis. Meloxicam is not dialyzable [see Dosage and Administration (2.1) and Use in Specific Populations (8.7)].

Drug Interaction Studies

Aspirin: When NSAIDs were administered with aspirin, the protein binding of NSAIDs were reduced, although the clearance of free NSAID was not altered. When meloxicam is administered with aspirin (1000 mg three times daily) to healthy volunteers, it tended to increase the AUC (10%) and Cmax (24%) of meloxicam. The clinical significance of this interaction is not known. See Table 3 for clinically significant drug interactions of NSAIDs with aspirin [see Drug Interactions (7)].

Cholestyramine: Pretreatment for four days with cholestyramine significantly increased the clearance of meloxicam by 50%. This resulted in a decrease in t 1/2 , from 19.2 hours to 12.5 hours, and a 35% reduction in AUC. This suggests the existence of a recirculation pathway for meloxicam in the gastrointestinal tract. The clinical relevance of this interaction has not been established.

Cimetidine: Concomitant administration of 200 mg cimetidine four times daily did not alter the single-dose pharmacokinetics of 30 mg meloxicam.

Digoxin: Meloxicam 15 mg once daily for 7 days did not alter the plasma concentration profile of digoxin after b-acetyldigoxin administration for 7 days at clinical doses. In vitro testing found no protein binding drug interaction between digoxin and meloxicam.

Lithium: In a study conducted in healthy subjects, mean pre-dose lithium concentration and AUC were increased by 21% in subjects receiving lithium doses ranging from 804 to 1072 mg twice daily with meloxicam 15 mg QD every day as compared to subjects receiving lithium alone [see Drug Interactions (7)].

Methotrexate: A study in 13 rheumatoid arthritis (RA) patients evaluated the effects of multiple doses of meloxicam on the pharmacokinetics of methotrexate taken once weekly. Meloxicam did not have a significant effect on the pharmacokinetics of single doses of methotrexate. In vitro, methotrexate did not displace meloxicam from its human serum binding sites [see Drug Interactions (7)].

Warfarin: The effect of meloxicam on the anticoagulant effect of warfarin was studied in a group of healthy subjects receiving daily doses of warfarin that produced an INR (International Normalized Ratio) between 1.2 and 1.8. In these subjects, meloxicam did not alter warfarin pharmacokinetics and the average anticoagulant effect of warfarin as determined by prothrombin time. However, one subject showed an increase in INR from 1.5 to 2.1. Caution should be used when administering Zybic™ with warfarin since patients on warfarin may experience changes in INR and an increased risk of bleeding complications when a new medication is introduced [see Drug Interactions (7)].

13 NONCLINICAL TOXICOLOGY

13.1 Carcinogenesis, Mutagenesis, Impairment of Fertility

Carcinogenesis

There was no increase in tumor incidence in long-term carcinogenicity studies in rats (104 weeks) and mice (99 weeks) administered meloxicam at oral doses up to 0.8 mg/kg/day in rats and up to 8.0 mg/kg/day in mice (up to 0.5-and 2.6-times, respectively, the maximum recommended human dose [MRHD] of 15 mg/day Zybic™ based on body surface area [BSA] comparison).

Mutagenesis

Meloxicam was not mutagenic in an Ames assay, or clastogenic in a chromosome aberration assay with human lymphocytes and an in vivo micronucleus test in mouse bone marrow.

Impairment of Fertility

Meloxicam did not impair male and female fertility in rats at oral doses up to 9 mg/kg/day in males and 5 mg/ kg/day in females (up to 5.8-and 3.2-times greater, respectively, than the MRHD based on BSA comparison).

14 CLINICAL STUDIES

14.1 Osteoarthritis and Rheumatoid Arthritis

The use of meloxicam for the treatment of the signs and symptoms of osteoarthritis of the knee and hip was evaluated in a 12-week, double-blind, controlled trial. Meloxicam (3.75 mg, 7.5 mg, and 15 mg daily) was compared to placebo. The four primary endpoints were investigator's global assessment, patient global assessment, patient pain assessment, and total WOMAC score (a self-administered questionnaire addressing pain, function, and stiffness). Patients on meloxicam 7.5 mg daily and meloxicam 15 mg daily showed significant improvement in each of these endpoints compared with placebo.

The use of meloxicam for the management of signs and symptoms of osteoarthritis was evaluated in six double-blind, active-controlled trials outside the U.S. ranging from 4 weeks' to 6 months' duration. In these trials, the efficacy of meloxicam, in doses of 7.5 mg/day and 15 mg/day, was comparable to piroxicam 20 mg/day and diclofenac SR 100 mg/day and consistent with the efficacy seen in the U.S. trial.

The use of meloxicam for the treatment of the signs and symptoms of rheumatoid arthritis was evaluated in a 12-week, double-blind, controlled multinational trial. Meloxicam (7.5 mg, 15 mg, and 22.5 mg daily) was compared to placebo. The primary endpoint in this study was the ACR20 response rate, a composite measure of clinical, laboratory, and functional measures of RA response. Patients receiving meloxicam 7.5 mg and 15 mg daily showed significant improvement in the primary endpoint compared with placebo. No incremental benefit was observed with the 22.5 mg dose compared to the 15 mg dose.

14.2 Juvenile Rheumatoid Arthritis (JRA) Pauciarticular and Polyarticular Course

The use of meloxicam for the treatment of the signs and symptoms of pauciarticular or polyarticular course Juvenile Rheumatoid Arthritis in patients 2 years of age and older was evaluated in two 12-week, double-blind, parallel-arm, active-controlled trials.

Both studies included three arms: naproxen and two doses of meloxicam. In both studies, meloxicam dosing began at 0.125 mg/kg/day (7.5 mg maximum) or 0.25 mg/kg/day (15 mg maximum), and naproxen dosing began at 10 mg/kg/day. One study used these doses throughout the 12-week dosing period, while the other incorporated a titration after 4 weeks to doses of 0.25 mg/kg/day and 0.375 mg/kg/day (22.5 mg maximum) of meloxicam and 15 mg/kg/day of naproxen.

The efficacy analysis used the ACR Pediatric 30 responder definition, a composite of parent and investigator assessments, counts of active joints and joints with limited range of motion, and erythrocyte sedimentation rate. The proportion of responders were similar in all three groups in both studies, and no difference was observed between the meloxicam dose groups.

16 HOW SUPPLIED/STORAGE AND HANDLING

Zybic™ is available as a yellowish green tinged viscous oral suspension containing 7.5 mg meloxicam in 5 mL.

Zybic™ 7.5 mg/5 mL: NDC 71741-228-10; Bottles of 100 mL

Storage

Store at 25°C (77°F); excursions permitted to 15° to 30°C (59° to 86°F) [see USP Controlled Room Temperature].

Keep oral suspension container tightly closed.

Keep this and all medications out of the reach of children.

17 PATIENT COUNSELING INFORMATION

Advise the patient to read the FDA-approved patient labeling (Medication Guide) that accompanies each prescription dispensed.

Inform patients, families or their caregivers of the following information before initiating therapy with an NSAID and periodically during the course of ongoing therapy.

Cardiovascular Thrombotic Events

Advise patients to be alert for the symptoms of cardiovascular thrombotic events, including chest pain, shortness of breath, weakness, or slurring of speech, and to report any of these symptoms to their healthcare provider immediately [see Warnings and Precautions (5.1)].

Gastrointestinal Bleeding, Ulceration, and Perforation

Advise patients to report symptoms of ulcerations and bleeding, including epigastric pain, dyspepsia, melena, and hematemesis to their healthcare provider. In the setting of concomitant use of low-dose aspirin for cardiac prophylaxis, inform patients of the increased risk for the signs and symptoms of GI bleeding [see Warnings and Precautions (5.2)].

Hepatotoxicity

Inform patients of the warning signs and symptoms of hepatotoxicity (e.g., nausea, fatigue, lethargy, diarrhea, pruritus, jaundice, right upper quadrant tenderness, and "flu-like" symptoms). If these occur, instruct patients to stop Zybic™ and seek immediate medical therapy [see Warnings and Precautions (5.3)].

Heart Failure and Edema

Advise patients to be alert for the symptoms of congestive heart failure including shortness of breath, unexplained weight gain, or edema and to contact their healthcare provider if such symptoms occur [see Warnings and Precautions (5.5)].

Anaphylactic Reactions

Inform patients of the signs of an anaphylactic reaction (e.g., difficulty breathing, swelling of the face or throat). Instruct patients to seek immediate emergency help if these occur [see Contraindications (4) and Warnings and Precautions (5.7)].

Serious Skin Reactions, including DRESS

Advise patients to stop taking Zybic™ immediately if they develop any type of rash or fever and to contact their healthcare provider as soon as possible [see Warnings and Precautions (5.9), (5.10)].

Female Fertility

Advise females of reproductive potential who desire pregnancy that NSAIDs, including Zybic™, may be associated with a reversible delay in ovulation [see Use in Specific Populations (8.3)].

Fetal Toxicity

Inform pregnant women to avoid use of Zybic™ and other NSAIDs starting at 30 weeks gestation because of the risk of the premature closing of the fetal ductus arteriosus. If treatment with Zybic™ is needed for a pregnant woman between about 20 to 30 weeks gestation, advise her that she may need to be monitored for oligohydramnios, if treatment continues for longer than 48 hours [see Warnings and Precautions (5.11) and Use in Specific Populations (8.1)].

Avoid Concomitant Use of NSAIDs

Inform patients that the concomitant use of Zybic™ with other NSAIDs or salicylates (e.g., diflunisal, salsalate) is not recommended due to the increased risk of gastrointestinal toxicity, and little or no increase in efficacy [see Warnings and Precautions (5.2) and Drug Interactions (7)]. Alert patients that NSAIDs may be present in "over the counter" medications for treatment of colds, fever, or insomnia.

Use of NSAIDs and Low-Dose Aspirin

Inform patients not to use low-dose aspirin concomitantly with Zybic™ until they talk to their healthcare provider [see Drug Interactions (7)].

For current prescribing information, call Redmont Pharmaceuticals, LLC at 800-528-3058.

Manufactured for Redmont Pharmaceuticals, LLC, Birmingham, AL 35209 USA

Made in Canada

© 2025 Redmont Pharmaceuticals, LLC

228111-1225

Medication Guide for Nonsteroidal Anti-inflammatory Drugs (NSAIDs)

What is the most important information I should know about medicines called Nonsteroidal Anti-inflammatory Drugs (NSAIDs)?

NSAIDs can cause serious side effects, including:

- Increased risk of a heart attack or stroke that can lead to death. This risk may happen early in treatment and may increase:
  - with increasing doses of NSAIDs
  - with longer use of NSAIDs

Do not take NSAIDs right before or after a heart surgery called a "coronary artery bypass graft (CABG)." Avoid taking NSAIDs after a recent heart attack, unless your healthcare provider tells you to. You may have an increased risk of another heart attack if you take NSAIDs after a recent heart attack.

- Increased risk of bleeding, ulcers, and tears (perforation) of the esophagus (tube leading from the mouth to the stomach), stomach and intestines:
  - anytime during use
  - without warning symptoms
  - that may cause death
  The risk of getting an ulcer or bleeding increases with:
  - past history of stomach ulcers, or stomach or intestinal bleeding with use of NSAIDs
  - taking medicines called "corticosteroids", "anticoagulants", "SSRIs", or "SNRIs"
  - increasing doses of NSAIDs
  - longer use of NSAIDs
  - smoking
  - drinking alcohol
  - older age
  - poor health
  - advanced liver disease
  - bleeding problems
  NSAIDs should only be used:
  - exactly as prescribed
  - at the lowest dose possible for your treatment
  - for the shortest time needed

What are NSAIDs?
NSAIDs are used to treat pain and redness, swelling, and heat (inflammation) from medical conditions such as different types of arthritis, menstrual cramps, and other types of short-term pain.

Who should not take NSAIDs?
Do not take NSAIDs:

- if you have had an asthma attack, hives, or other allergic reaction with aspirin or any other NSAIDs.
- right before or after heart bypass surgery.

Before taking NSAIDs, tell your healthcare provider about all of your medical conditions, including if you:

- have liver or kidney problems
- have high blood pressure
- have asthma
- are pregnant or plan to become pregnant. Taking NSAIDs at about 20 weeks of pregnancy or later may harm your unborn baby. If you need to take NSAIDs for more than 2 days when you are between 20 and 30 weeks of pregnancy, your healthcare provider may need to monitor the amount of fluid in your womb and around your baby. You should not take NSAIDs after about 30 weeks of pregnancy.
- are breastfeeding or plan to breast feed.

Tell your healthcare provider about all of the medicines you take, including prescription or over-the-counter medicines, vitamins or herbal supplements. NSAIDs and some other medicines can interact with each other and cause serious side effects.
Do not start taking any new medicine without talking to your healthcare provider first.

What are the possible side effects of NSAIDs?
NSAIDs can cause serious side effects, including:
See "What is the most important information I should know about medicines called Nonsteroidal Anti-inflammatory Drugs (NSAIDs)?"

- new or worse high blood pressure
- heart failure
- liver problems including liver failure
- kidney problems including kidney failure
- low red blood cells (anemia)
- life-threatening skin reactions
- life-threatening allergic reactions
- Other side effects of NSAIDs include: stomach pain, constipation, diarrhea, gas, heartburn, nausea, vomiting, and dizziness.

Get emergency help right away if you get any of the following symptoms:

- shortness of breath or trouble breathing
- chest pain
- weakness in one part or side of your body
- slurred speech
- swelling of the face or throat

Stop taking your NSAID and call your healthcare provider right away if you get any of the following symptoms:

- nausea
- more tired or weaker than usual
- diarrhea
- itching
- your skin or eyes look yellow
- indigestion or stomach pain
- flu-like symptoms
- vomit blood
- there is blood in your bowel movement or it is black and sticky like tar
- unusual weight gain
- skin rash or blisters with fever
- swelling of the arms, legs, hands and feet

If you take too much of your NSAID, call your healthcare provider or get medical help right away.
These are not all the possible side effects of NSAIDs. For more information, ask your healthcare provider or pharmacist about NSAIDs.
Call your doctor for medical advice about side effects. You may report side effects to FDA at 1-800-FDA-1088.

Other information about NSAIDs:

- Aspirin is an NSAID but it does not increase the chance of a heart attack. Aspirin can cause bleeding in the brain, stomach, and intestines. Aspirin can also cause ulcers in the stomach and intestines.
- Some NSAIDs are sold in lower doses without a prescription (over-the-counter). Talk to your healthcare provider before using over-the-counter NSAIDs for more than 10 days.

General information about the safe and effective use of NSAIDs
Medicines are sometimes prescribed for purposes other than those listed in a Medication Guide. Do not use NSAIDs for a condition for which it was not prescribed. Do not give NSAIDs to other people, even if they have the same symptoms that you have. It may harm them.
If you would like more information about NSAIDs, talk with your healthcare provider. You can ask your pharmacist or healthcare provider for information about NSAIDs that is written for health professionals.

Manufactured for Redmont Pharmaceuticals, LLC, Birmingham, AL 35209 USA
Made in Canada
© 2025 Redmont Pharmaceuticals, LLC

This Medication Guide has been approved by the U.S. Food and Drug Administration.
Revised: September 2025

PRINCIPAL DISPLAY PANEL - 100 mL Bottle Label

NDC 71741-228-10
100 mL

ATTENTION DISPENSER:
Accompanying Medication Guide
must be dispensed with this product.

Zybic™
(Meloxicam
Oral Suspension, USP)
7.5 mg/5 mL

Rx Only

REDMONT
PHARMACEUTICALS